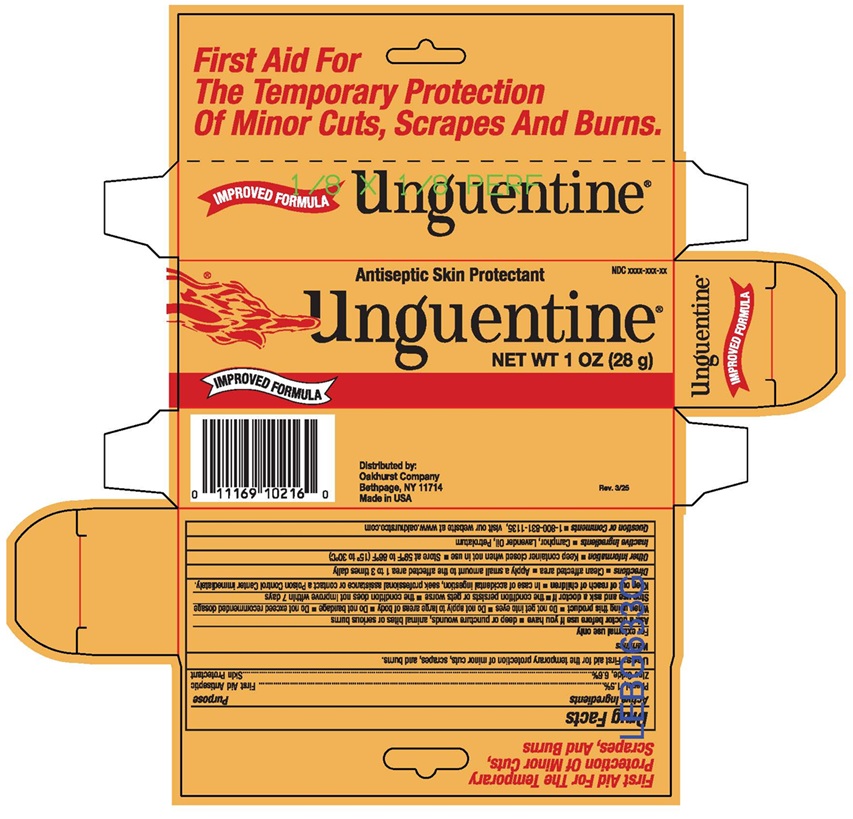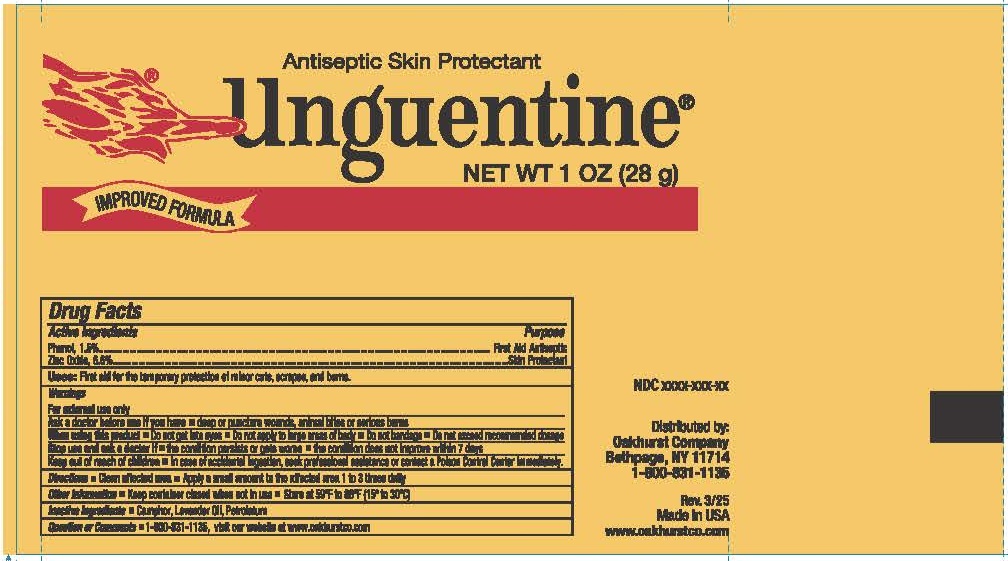 DRUG LABEL: Unguentine
NDC: 45728-446 | Form: OINTMENT
Manufacturer: Oakhurst Company
Category: otc | Type: HUMAN OTC DRUG LABEL
Date: 20250410

ACTIVE INGREDIENTS: PHENOL 0.015 g/1 g; ZINC OXIDE 0.066 g/1 g
INACTIVE INGREDIENTS: CINNAMOMUM CAMPHORA WHOLE; LAVENDER OIL; PETROLATUM

Unguentine

Active Ingredients

Phenol, 1.5%

Purpose

First Aid Antiseptic

Active Ingredients

Zinc Oxide, 6.6%

Purpose

Skin Protectant

Uses

First aid for the temporary protection of minor cuts, scrapes, and burns.

Warnings

For external use only

Ask a doctor before use if you have

- deep or puncture wounds, animal bites or serious burns

When using this product

- Do not get into eyes
- Do not apply to large areas of body
- Do not bandage
- Do not exceed recommended dosage

Stop use and ask a docter if

- the condition persists or gets worse
- the condition does not improve within 7 days

Keep out of reach of children

- In case of accidental ingestion, seel professional assistance or contact a Poison Control Center immediately.

Directions

- Clean affected area
- Apply a small amount to the affected area 1 to 3 times daily

Other Information

- Keep container closed when not in use
- Store at 59°F to 86°F (15° to 30°C)

Inactive Ingredients

Camphor, Lavender Oil, Petrolatum

Question or Comments

- 1-800-831-1135, visit our website at www.oakhurstco.com